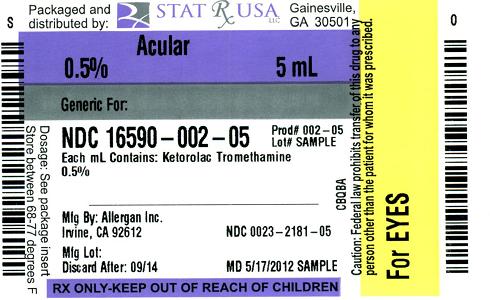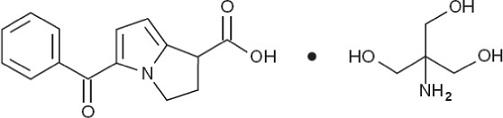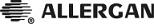 DRUG LABEL: ACULAR
NDC: 16590-002 | Form: SOLUTION/ DROPS
Manufacturer: STAT Rx USA LLC
Category: prescription | Type: HUMAN PRESCRIPTION DRUG LABEL
Date: 20120531

ACTIVE INGREDIENTS: KETOROLAC TROMETHAMINE 5 mg/1 mL
INACTIVE INGREDIENTS: BENZALKONIUM CHLORIDE; EDETATE DISODIUM; OCTOXYNOL-40; WATER; SODIUM CHLORIDE; HYDROCHLORIC ACID; SODIUM HYDROXIDE

ACULAR®
(ketorolac tromethamine ophthalmic solution) 0.5%
sterile

DESCRIPTION

ACULAR® (ketorolac tromethamine ophthalmic solution) is a member of the pyrrolo-pyrrole group of nonsteroidal anti-inflammatory drugs (NSAIDs) for ophthalmic use. Its chemical name is (±)-5-Benzoyl-2,3-dihydro-1H-pyrrolizine-1-carboxylic acid, compound with 2-amino-2-(hydroxymethyl)-1,3-propanediol (1:1) and it has the following structure:

ACULAR® ophthalmic solution is supplied as a sterile isotonic aqueous 0.5% solution, with a pH of 7.4. ACULAR® ophthalmic solution is a racemic mixture of R-(+) and S-(-)- ketorolac tromethamine. Ketorolac tromethamine may exist in three crystal forms. All forms are equally soluble in water. The pKa of ketorolac is 3.5. This white to off-white crystalline substance discolors on prolonged exposure to light. The molecular weight of ketorolac tromethamine is 376.40. The osmolality of ACULAR® ophthalmic solution is 290 mOsml/kg.

Each mL of ACULAR® ophthalmic solution contains: Active: ketorolac tromethamine 0.5%. Preservative: benzalkonium chloride 0.01%. Inactives: edetate disodium 0.1%; octoxynol 40; purified water; sodium chloride; and hydrochloric acid and/or sodium hydroxide to adjust pH.

CLINICAL PHARMACOLOGY

Ketorolac tromethamine is a nonsteroidal anti-inflammatory drug which, when administered systemically, has demonstrated analgesic, anti-inflammatory, and anti-pyretic activity. The mechanism of its action is thought to be due to its ability to inhibit prostaglandin biosynthesis. Ketorolac tromethamine given systemically does not cause pupil constriction.

Prostaglandins have been shown in many animal models to be mediators of certain kinds of intraocular inflammation. In studies performed in animal eyes, prostaglandins have been shown to produce disruption of the blood-aqueous humor barrier, vasodilation, increased vascular permeability, leukocytosis, and increased intraocular pressure. Prostaglandins also appear to play a role in the miotic response produced during ocular surgery by constricting the iris sphincter independently of cholinergic mechanisms.

Two drops (0.1 mL) of 0.5% ACULAR® ophthalmic solution instilled into the eyes of patients 12 hours and 1 hour prior to cataract extraction achieved measurable levels in 8 of 9 patients' eyes (mean ketorolac concentration 95 ng/mL aqueous humor, range 40 to 170 ng/mL). Ocular administration of ketorolac tromethamine reduces prostaglandin E2 (PGE2) levels in aqueous humor. The mean concentration of PGE2 was 80 pg/mL in the aqueous humor of eyes receiving vehicle and 28 pg/mL in the eyes receiving ACULAR® 0.5% ophthalmic solution.

One drop (0.05 mL) of 0.5% ACULAR® ophthalmic solution was instilled into one eye and one drop of vehicle into the other eye TID in 26 normal subjects. Only 5 of 26 subjects had a detectable amount of ketorolac in their plasma (range 10.7 to 22.5 ng/mL) at Day 10 during topical ocular treatment. When ketorolac tromethamine 10 mg is administered systemically every 6 hours, peak plasma levels at steady state are around 960 ng/mL.

Two controlled clinical studies showed that ACULAR® ophthalmic solution was significantly more effective than its vehicle in relieving ocular itching caused by seasonal allergic conjunctivitis.

Two controlled clinical studies showed that patients treated for two weeks with ACULAR® ophthalmic solution were less likely to have measurable signs of inflammation (cell and flare) than patients treated with its vehicle.

Results from clinical studies indicate that ketorolac tromethamine has no significant effect upon intraocular pressure; however, changes in intraocular pressure may occur following cataract surgery.

INDICATIONS AND USAGE

ACULAR® ophthalmic solution is indicated for the temporary relief of ocular itching due to seasonal allergic conjunctivitis. ACULAR® ophthalmic solution is also indicated for the treatment of postoperative inflammation in patients who have undergone cataract extraction.

CONTRAINDICATIONS

ACULAR® ophthalmic solution is contraindicated in patients with previously demonstrated hypersensitivity to any of the ingredients in the formulation.

WARNINGS

There is the potential for cross-sensitivity to acetylsalicylic acid, phenylacetic acid derivatives, and other nonsteroidal anti-inflammatory agents. Therefore, caution should be used when treating individuals who have previously exhibited sensitivities to these drugs.

With some nonsteroidal anti-inflammatory drugs, there exists the potential for increased bleeding time due to interference with thrombocyte aggregation. There have been reports that ocularly applied nonsteroidal anti-inflammatory drugs may cause increased bleeding of ocular tissues (including hyphemas) in conjunction with ocular surgery.

PRECAUTIONS

General

All topical nonsteroidal anti-inflammatory drugs (NSAIDs) may slow or delay healing. Topical corticosteroids are also known to slow or delay healing. Concomitant use of topical NSAIDs and topical steroids may increase the potential for healing problems.

Use of topical NSAIDs may result in keratitis. In some susceptible patients, continued use of topical NSAIDs may result in epithelial breakdown, corneal thinning, corneal erosion, corneal ulceration or corneal perforation. These events may be sight threatening. Patients with evidence of corneal epithelial breakdown should immediately discontinue use of topical NSAIDs and should be closely monitored for corneal health.

Postmarketing experience with topical NSAIDs suggests that patients with complicated ocular surgeries, corneal denervation, corneal epithelial defects, diabetes mellitus, ocular surface diseases (e.g., dry eye syndrome), rheumatoid arthritis, or repeat ocular surgeries within a short period of time may be at increased risk for corneal adverse events which may become sight threatening. Topical NSAIDs should be used with caution in these patients.

Postmarketing experience with topical NSAIDs also suggests that use more than 24 hours prior to surgery or use beyond 14 days post-surgery may increase patient risk for the occurrence and severity of corneal adverse events.

It is recommended that ACULAR® ophthalmic solution be used with caution in patients with known bleeding tendencies or who are receiving other medications which may prolong bleeding time.

PATIENT COUNSELING INFORMATION

Information for Patients: ACULAR® ophthalmic solution should not be administered while wearing contact lenses.

Carcinogenesis, Mutagenesis, Impairment of Fertility

Ketorolac tromethamine was not carcinogenic in rats given up to 5 mg/kg/day orally for 24 months (151 times the maximum recommended human topical ophthalmic dose, on a mg/kg basis, assuming 100% absorption in humans and animals) nor in mice given 2 mg/kg/day orally for 18 months (60 times the maximum recommended human topical ophthalmic dose, on a mg/kg basis, assuming 100% absorption in humans and animals).

Ketorolac tromethamine was not mutagenic in vitro in the Ames assay or in forward mutation assays. Similarly, it did not result in an in vitro increase in unscheduled DNA synthesis or an in vivo increase in chromosome breakage in mice. However, ketorolac tromethamine did result in an increased incidence in chromosomal aberrations in Chinese hamster ovary cells.

Ketorolac tromethamine did not impair fertility when administered orally to male and female rats at doses up to 272 and 484 times the maximum recommended human topical ophthalmic dose, respectively, on a mg/kg basis, assuming 100% absorption in humans and animals.

Pregnancy

TERATOGENIC EFFECTS

Teratogenic Effects: Pregnancy Category C. Ketorolac tromethamine, administered during organogenesis, was not teratogenic in rabbits or rats at oral doses up to 109 times and 303 times the maximum recommended human topical ophthalmic dose, respectively, on a mg/kg basis assuming 100% absorption in humans and animals. When administered to rats after Day 17 of gestation at oral doses up to 45 times the maximum recommended human topical ophthalmic dose, respectively, on a mg/kg basis, assuming 100% absorption in humans and animals, ketorolac tromethamine resulted in dystocia and increased pup mortality. There are no adequate and well-controlled studies in pregnant women. ACULAR® ophthalmic solution should be used during pregnancy only if the potential benefit justifies the potential risk to the fetus.

NONTERATOGENIC EFFECTS

Nonteratogenic Effects: Because of the known effects of prostaglandin-inhibiting drugs on the fetal cardiovascular system (closure of the ductus arteriosus), the use of ACULAR® ophthalmic solution during late pregnancy should be avoided.

Nursing Mothers

Caution should be exercised when ACULAR® ophthalmic solution is administered to a nursing woman.

Pediatric Use

Safety and efficacy in pediatric patients below the age of 3 have not been established.

Geriatric Use

No overall differences in safety or effectiveness have been observed between elderly and younger patients.

ADVERSE REACTIONS

The most frequent adverse events reported with the use of ketorolac tromethamine ophthalmic solutions have been transient stinging and burning on instillation. These events were reported by up to 40% of patients participating in clinical trials.

Other adverse events occurring approximately 1% - 10% of the time during treatment with ketorolac tromethamine ophthalmic solutions included allergic reactions, corneal edema, iritis, ocular inflammation, ocular irritation, superficial keratitis, and superficial ocular infections.

Other adverse events reported rarely with the use of ketorolac tromethamine ophthalmic solutions included: corneal infiltrates, corneal ulcer, eye dryness, headaches, and visual disturbance (blurry vision).

CLINICAL STUDIES

Clinical Practice: The following events have been identified during postmarketing use of ketorolac tromethamine ophthalmic solution 0.5% in clinical practice. Because they are reported voluntarily from a population of unknown size, estimates of frequency cannot be made. The events, which have been chosen for inclusion due to either their seriousness, frequency of reporting, possible causal connection to topical ketorolac tromethamine ophthalmic solution 0.5%, or a combination of these factors, include corneal erosion, corneal perforation, corneal thinning and epithelial breakdown (see PRECAUTIONS, General).

DOSAGE AND ADMINISTRATION

The recommended dose of ACULAR® ophthalmic solution is one drop (0.25 mg) four times a day for relief of ocular itching due to seasonal allergic conjunctivitis.

For the treatment of postoperative inflammation in patients who have undergone cataract extraction, one drop of ACULAR® ophthalmic solution should be applied to the affected eye(s) four times daily beginning 24 hours after cataract surgery and continuing through the first 2 weeks of the postoperative period.

ACULAR® ophthalmic solution has been safely administered in conjunction with other ophthalmic medications such as antibiotics, beta blockers, carbonic anhydrase inhibitors, cycloplegics, and mydriatics.

HOW SUPPLIED

ACULAR® (ketorolac tromethamine ophthalmic solution) is supplied sterile in opaque white LDPE plastic bottles with white droppers with gray high impact polystyrene (HIPS) caps as follows:

5 mL in 10 mL bottle - NDC 16590-002-05

Store at 15°C - 25°C (59°F- 77°F) with protection from light.

Rx Only

Revised: 05/2011

© 2011 Allergan, Inc.

Irvine, CA 92612, U.S.A.

ACULAR® is manufactured and distributed by Allergan, Inc. under license from its developer, Roche Palo Alto LLC, Palo Alto, CA, U.S.A.
® marks owned by Allergan, Inc.
Made in the U.S.A.

71590US13C

Relabeling and Repackaging by:
STAT Rx USA LLC
Gainesville, GA 30501

PACKAGE LABEL

ACULAR® Rx only

(ketorolac tromethamine ophthalmic solution) 0.5%

sterile 5 mL